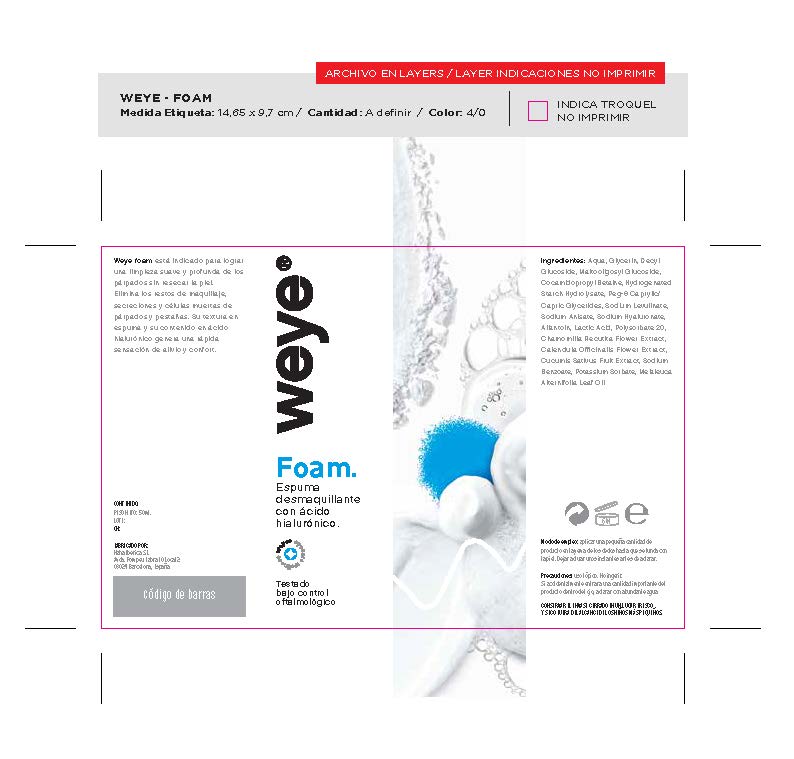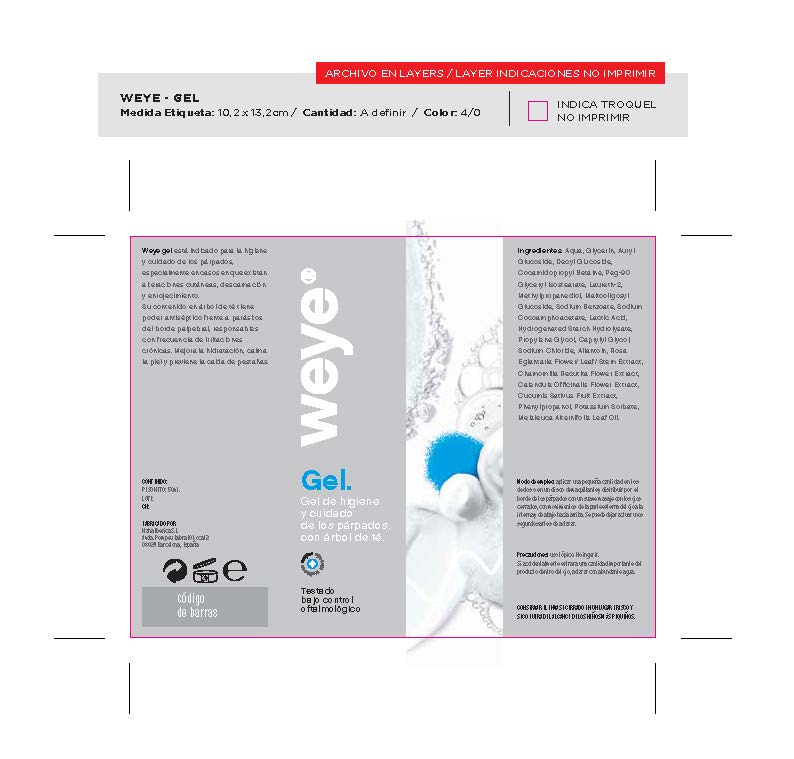 DRUG LABEL: DESMAQUILLANTE OJOS WEYE
NDC: 82222-001 | Form: CREAM
Manufacturer: WEYE LABORATORY GROUP S.L.
Category: otc | Type: HUMAN OTC DRUG LABEL
Date: 20210907

ACTIVE INGREDIENTS: GLYCERIN 1 U/1 U
INACTIVE INGREDIENTS: LACTIC ACID 1 U/1 U; POLYSORBATE 20 1 U/1 U; SODIUM BENZOATE 1 U/1 U; WATER 1 U/1 U; DECYL GLUCOSIDE 1 U/1 U; COCAMIDOPROPYL BETAINE 1 U/1 U; PEG-9 DIGLYCIDYL ETHER/SODIUM HYALURONATE CROSSPOLYMER 1 U/1 U; ALLANTOIN 1 U/1 U; SODIUM LEVULINATE 1 U/1 U; SODIUM ANISATE 1 U/1 U; POTASSIUM SORBATE 1 U/1 U; MELALEUCA ALTERNIFOLIA LEAF 1 U/1 U; MALTOOLIGOSYL GLUCOSIDE 1 U/1 U; HYDROGENATED STARCH HYDROLYSATE 1 U/1 U; PEG-6 CAPRYLIC/CAPRIC GLYCERIDES 1 U/1 U; MATRICARIA CHAMOMILLA FLOWERING TOP 1 U/1 U; CALENDULA OFFICINALIS FLOWER 1 U/1 U; CUCUMIS SATIVUS LEAF 1 U/1 U

ACTIVE INGREDIENT

PURPOSE

PURPOSE AND USES

WARNINGS AND PRECAUTION

WARNINGS

ASK DOCTOR

KEEP OUT

QUESTIONS

PREGNANCY

PREGNANCY WARNING

indications

dosage

inactive ingredients

indications and usage

PRINCIPAL DISPLAY PANEL